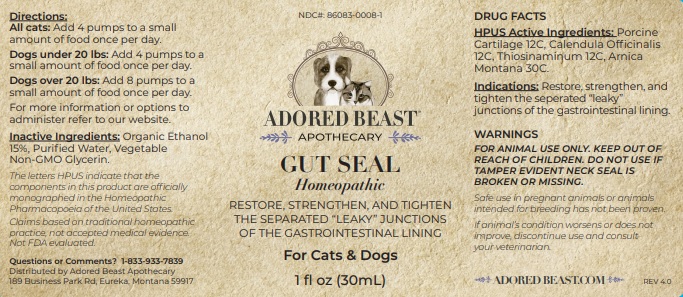 DRUG LABEL: GUT SEAL
NDC: 86083-0008 | Form: LIQUID
Manufacturer: The Adored Beast Apothecary, Ltd
Category: homeopathic | Type: OTC ANIMAL DRUG LABEL
Date: 20251027

ACTIVE INGREDIENTS: SUS SCROFA CARTILAGE 12 [hp_C]/30 mL; CALENDULA OFFICINALIS WHOLE 12 [hp_C]/30 mL; ALLYLTHIOUREA 12 [hp_C]/30 mL; ARNICA MONTANA WHOLE 30 [hp_C]/30 mL
INACTIVE INGREDIENTS: ALCOHOL; WATER; GLYCERIN

GUT SEAL

DRUG FACTS
HPUS Active Ingredients: Porcine Cartilage 12C, Calendula Officinalis 12C, Thiosinaminum 12C, Arnica Montana 30C.

The letters HPUS indicate that the components in this product are officially monographed in the Homeopathic Pharmacopoeia of the United States.
Claims based on traditional homeopathic practice, not accepted medical evidence. Not FDA evaluated.

INDICATIONS AND USAGE

Indications: Restore, strengthen, and tighten the seperated “leaky” junctions of the gastrointestinal lining.

WARNINGS
FOR ANIMAL USE ONLY. KEEP OUT OF REACH OF CHILDREN. DO NOT USE IF
TAMPER EVIDENT NECK SEAL IS BROKEN OR MISSING.

KEEP OUT OF REACH OF CHILDREN

DOSAGE AND ADMINISTRATION

Indications: Restore, strengthen, and tighten the seperated “leaky junctions of the gastrointestinal lining.

INACTIVE INGREDIENT

Inactive Ingredients: Organic Ethanol 15%, Purified Water, Vegetable Non-GMO Glycerin

Questions or Comments? 1-833-933-7839

Distributed by Adored Beast Apothecary

189 Business Park Rd, Eureka, Montana 59917

OTHER SAFETY INFORMATION

Safe use in pregnant animals or animals
intended for breeding has not been proven.

If animal’s condition worsens or does not
improve, discontinue use and consult
your veterinarian.

PACKAGE LABEL

NDC#: 86083-0008-1

ADORED BEAST

APOTHECARY

GUT STEAL

Homeopathic

RESTORE, STRENGTHEN, AND TIGHTEN THE SEPARATED "LEAKY" JUNCTIONS OF THE GASTROINTESTINAL LINING.

For Cats & Dogs

1 fl oz (30mL)

PURPOSE

Restore, strengthen, and tighten the seperated "leaky" junctions of the gastrointestinal lining.